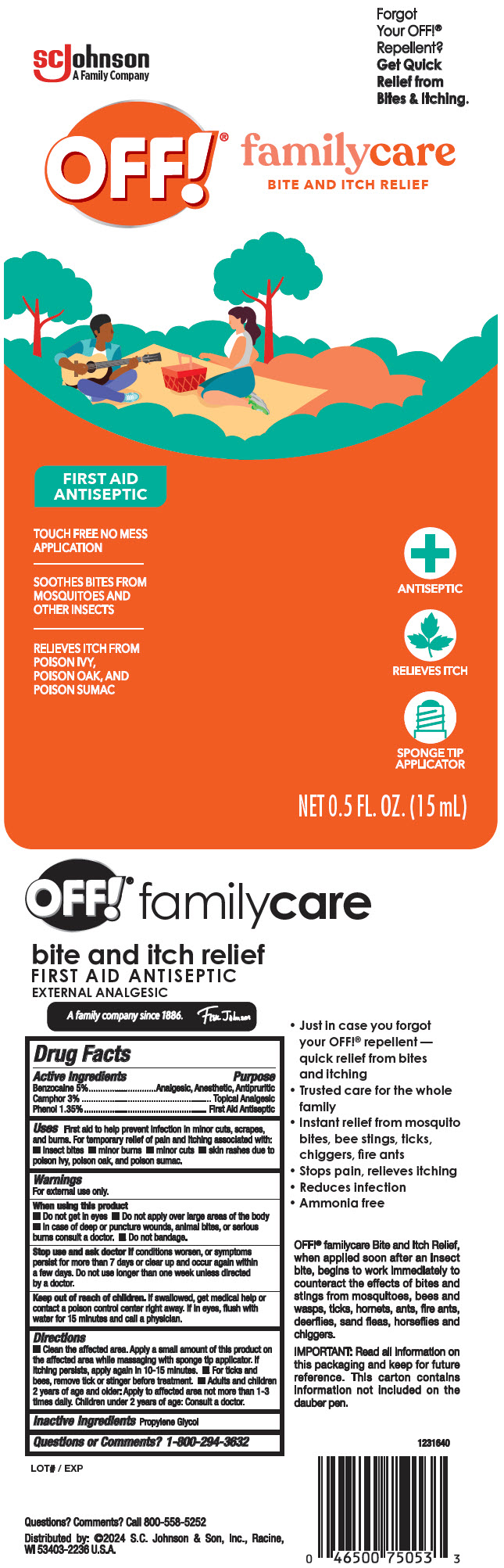 DRUG LABEL: OFF Bite and Itch Relief First Aid Antiseptic
NDC: 59397-3310 | Form: SOLUTION
Manufacturer: S. C. Johnson & Son, Inc.
Category: otc | Type: HUMAN OTC DRUG LABEL
Date: 20240607

ACTIVE INGREDIENTS: BENZOCAINE 5 mg/100 mL; PHENOL 1.35 mg/100 mL; CAMPHOR (NATURAL) 3 mg/100 mL
INACTIVE INGREDIENTS: PROPYLENE GLYCOL

OFF® Bite and Itch Relief First Aid Antiseptic

Drug Facts

ACTIVE INGREDIENT

Active Ingredients | Purpose
Benzocaine 5% | Analgesic, Anesthetic, Antipruritic
Camphor 3% | Topical Analgesic
Phenol 1.35% | First Aid Antiseptic

Uses

First aid to help prevent infection in minor cuts, scrapes, and burns. For temporary relief of pain and itching associated with:

- insect bites
- minor burns
- minor cuts
- skin rashes due to poison ivy, poison oak, and poison sumac.

Warnings

For external use only.

When using this product

- Do not get in eyes
- Do not apply over large areas of the body
- In case of deep or puncture wounds, animal bites, or serious burns consult a doctor.
- Do not bandage.

Stop use and ask doctor if conditions worsen, or symptoms persist for more than 7 days or clear up and occur again within a few days. Do not use longer than one week unless directed by a doctor.

Keep out of reach of children. If swallowed, get medical help or contact a poison control center right away. If in eyes, flush with water for 15 minutes and call a physician.

Directions

- Clean the affected area. Apply a small amount of this product on the affected area while massaging with sponge tip applicator. If itching persists, apply again in 10-15 minutes.
- For ticks and bees, remove tick or stinger before treatment.
- Adults and children 2 years of age and older: Apply to affected area not more than 1-3 times daily. Children under 2 years of age: Consult a doctor.

Inactive Ingredients

Propylene Glycol

Questions or Comments?

1-800-294-3632

Distributed by: ©2024 S.C. Johnson & Son, Inc., Racine,
WI 53403-2236 U.S.A.

PRINCIPAL DISPLAY PANEL - 15 mL Bottle Label

SCJohnson
A Family Company

Forgot
Your OFF!®
Repellent?
Get Quick
Relief from
Bites & Itching.

OFF!®

familycare
BITE AND ITCH RELIEF

FIRST AID
ANTISEPTIC

TOUCH FREE NO MESS
APPLICATION

SOOTHES BITES FROM
MOSQUITOES AND
OTHER INSECTS

RELIEVES ITCH FROM
POISON IVY,
POISON OAK, AND
POISON SUMAC

ANTISEPTIC

RELIEVES ITCH

SPONGE TIP
APPLICATOR

NET 0.5 FL. OZ. (15 mL)